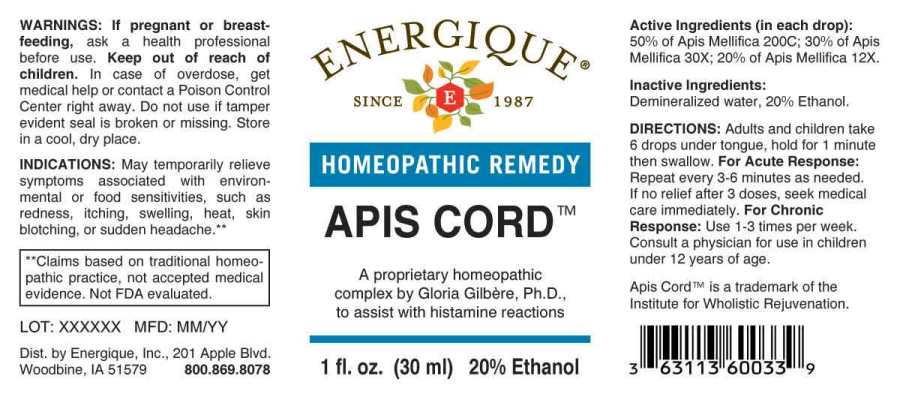 DRUG LABEL: Apis Cord
NDC: 44911-0463 | Form: LIQUID
Manufacturer: Energique, Inc.
Category: homeopathic | Type: HUMAN OTC DRUG LABEL
Date: 20240716

ACTIVE INGREDIENTS: APIS MELLIFERA 12 [hp_X]/1 mL
INACTIVE INGREDIENTS: WATER; ALCOHOL

DRUG FACTS:

ACTIVE INGREDIENTS:

(in each drop): 50% of Apis Mellifica 200C; 30% Apis Mellifica 30X; 20% of Apis Mellifica 12X.

INDICATIONS:

May temporarily relieve symptoms associated with environmental or food sensitivities, such as redness, itching, swelling, heat, skin blotching, or sudden headache.

**Claims based on traditional homeopathic practice, not accepted medical evidence. Not FDA evaluated.

WARNINGS:

If pregnant or breast-feeding, ask a health professional before use.

Keep out of reach of children. In case of overdose, get medical help or contact a Poison Control Center right away.

Do not use if tamper evident seal is broken or missing. Store in a cool, dry place.

KEEP OUT OF REACH OF CHILDREN:

In case of overdose, get medical help or contact a Poison Control Center right away.

DIRECTIONS:

Adults and children take 6 drops under the tongue, hold for 1 minute then swallow.

For Acute Response: Repeat every 3-6 minutes as needed. If no relief after 3 doses, seek medical care immediately.

For Chronic Response: Use 1-3 times per week.

Consult a physician for use in children under 12 years of age.

INDICATIONS:

May temporarily relieve symptoms associated with environmental or food sensitivities, such as redness, itching, swelling, heat, skin blotching, or sudden headache.

**Claims based on traditional homeopathic practice, not accepted medical evidence. Not FDA evaluated.

INACTIVE INGREDIENTS:

Demineralized water, 20% Ethanol.

QUESTIONS:

Dist. by Energique, Inc.

201 Apple Blvd

Woodbine, IA 51579 800.869.8078

Apis Cord™ is a trademark of the Institute for Wholistic Rejuvenation.

PACKAGE LABEL DISPLAY:

ENERGIQUE

SINCE 1987

HOMEOPATHIC REMEDY

APIS CORD™

A proprietary homeopathic

complex by Gloria Gilbère, Ph.D.

to assist with histamine responses

1 fl. oz. (30 ml)